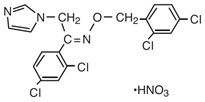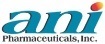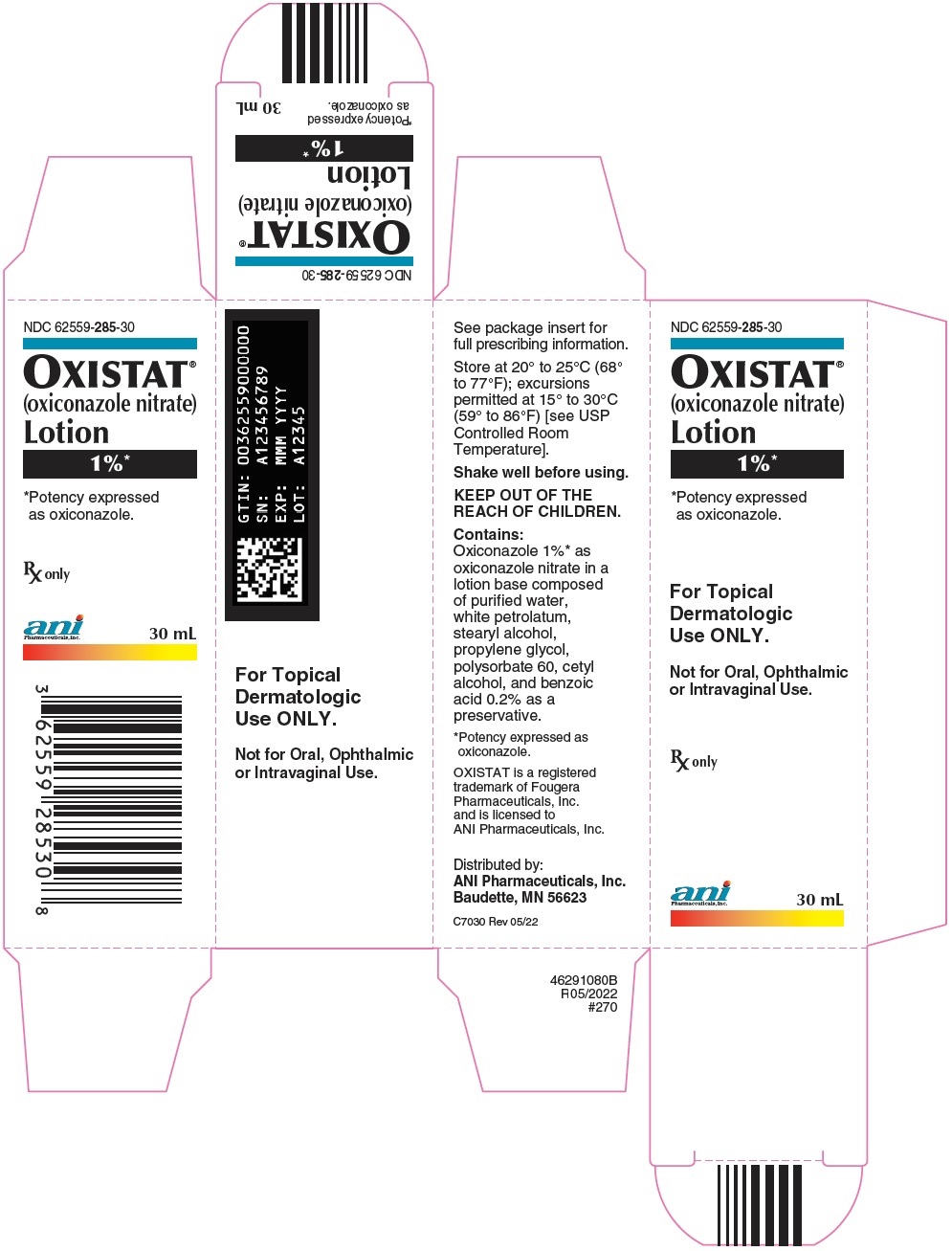 DRUG LABEL: Oxistat
NDC: 62559-285 | Form: LOTION
Manufacturer: ANI Pharmaceuticals, Inc.
Category: prescription | Type: HUMAN PRESCRIPTION DRUG LABEL
Date: 20250724

ACTIVE INGREDIENTS: oxiconazole nitrate 10 mg/1 mL
INACTIVE INGREDIENTS: water; stearyl alcohol; propylene glycol; polysorbate 60; cetyl alcohol; benzoic acid; WHITE PETROLATUM

OXISTAT® (oxiconazole nitrate) Lotion, 1%*

*Potency expressed as oxiconazole

Rx only

FOR TOPICAL DERMATOLOGIC USE ONLY—
NOT FOR ORAL, OPHTHALMIC OR INTRAVAGINAL USE

DESCRIPTION

OXISTAT® (oxiconazole nitrate) Lotion, 1% contains the antifungal active compound oxiconazole nitrate. This formulation is for topical dermatologic use only.

Chemically, oxiconazole nitrate is 2',4'-dichloro-2-imidazol-1-ylacetophenone (Z)-[0-(2,4-dichlorobenzyl)oxime], mononitrate. The compound has the molecular formula C18H13ON3Cl4·HNO3, a molecular weight of 492.15, and the following structural formula:

Oxiconazole nitrate is a nearly white crystalline powder, soluble in methanol; sparingly soluble in ethanol, chloroform, and acetone; and very slightly soluble in water.

OXISTAT Lotion contains 10 mg of oxiconazole per gram of lotion in a white to off-white, opaque lotion base of purified water, white petrolatum, stearyl alcohol, propylene glycol, polysorbate 60, cetyl alcohol, and benzoic acid 0.2% as a preservative.

CLINICAL PHARMACOLOGY

Pharmacokinetics

The penetration of oxiconazole nitrate into different layers of the skin was assessed using an in vitro permeation technique with human skin. Five hours after application of 2.5 mg/cm^2 of oxiconazole nitrate cream onto human skin, the concentration of oxiconazole nitrate was demonstrated to be 16.2 μmol in the epidermis, 3.64 μmol in the upper corium, and 1.29 μmol in the deeper corium. Systemic absorption of oxiconazole nitrate is low. Using radiolabeled drug, less than 0.3% of the applied dose of oxiconazole nitrate was recovered in the urine of volunteer subjects up to 5 days after application of the cream formulation.

Neither in vitro nor in vivo studies have been conducted to establish relative activity between the lotion and cream formulations.

Microbiology

Oxiconazole nitrate is an imidazole derivative whose antifungal activity is derived primarily from the inhibition of ergosterol biosynthesis, which is critical for cellular membrane integrity. It has in vitro activity against a wide range of pathogenic fungi.

Oxiconazole has been shown to be active against most strains of the following organisms both in vitro and in clinical infections at indicated body sites (see INDICATIONS AND USAGE):

Epidermophyton floccosum
Trichophyton mentagrophytes
Trichophyton rubrum
Malassezia furfur

The following in vitro data are available; however, their clinical significance is unknown. Oxiconazole exhibits satisfactory in vitro minimum inhibitory concentrations (MICs) against most strains of the following organisms; however, the safety and efficacy of oxiconazole in treating clinical infections due to these organisms have not been established in adequate and well-controlled clinical trials:

Candida albicans
Microsporum audouini
Microsporum canis
Microsporum gypseum
Trichophyton tonsurans
Trichophyton violaceum

INDICATIONS AND USAGE

OXISTAT Lotion is indicated for the topical treatment of the following dermal infections: tinea pedis, tinea cruris, and tinea corporis due to Trichophyton rubrum, Trichophyton mentagrophytes, or Epidermophyton floccosum (see DOSAGE AND ADMINISTRATION and CLINICAL STUDIES).

CONTRAINDICATIONS

OXISTAT Lotion is contraindicated in individuals who have shown hypersensitivity to any of their components.

WARNINGS

OXISTAT (oxiconazole nitrate) Lotion, 1% is for topical use only and not for oral, ophthalmic or intravaginal use.

PRECAUTIONS

General

OXISTAT Lotion is for external dermal use only. Avoid introduction of OXISTAT Lotion into the mouth, eyes, or vagina. If a reaction suggesting sensitivity or chemical irritation should occur with the use of OXISTAT Lotion, treatment should be discontinued and appropriate therapy instituted. If signs of epidermal irritation should occur, the drug should be discontinued.

Information for Patients

The patient should be instructed to:

1. Use OXISTAT as directed by the physician. The hands should be washed after applying the medication to the affected area(s). Avoid contact with the eyes, nose, mouth, and other mucous membranes. OXISTAT is for external use only.
2. Use the medication for the full treatment time recommended by the physician, even though symptoms may have improved. Notify the physician if there is no improvement after 2 to 4 weeks, or sooner if the condition worsens (see below).
3. Inform the physician if the area of application shows signs of increased irritation, itching, burning, blistering, swelling, or oozing.
4. Avoid the use of occlusive dressings unless otherwise directed by the physician.
5. Do not use this medication for any disorder other than that for which it was prescribed.

Drug Interactions

Potential drug interactions between OXISTAT and other drugs have not been systematically evaluated.

Carcinogenesis, Mutagenesis, Impairment of Fertility

Although no long-term studies in animals have been performed to evaluate carcinogenic potential, no evidence of mutagenic effect was found in 2 mutation assays (Ames test and Chinese hamster V79 in vitro cell mutation assay) or in 2 cytogenetic assays (human peripheral blood lymphocyte in vitro chromosome aberration assay and in vivo micronucleus assay in mice).

Reproductive studies revealed no impairment of fertility in rats at oral doses of 3 mg/kg/day in females (1 time the human dose based on mg/m^2) and 15 mg/kg/day in males (4 times the human dose based on mg/m^2). However, at doses above this level, the following effects were observed: a reduction in the fertility parameters of males and females, a reduction in the number of sperm in vaginal smears, extended estrous cycle, and a decrease in mating frequency.

Pregnancy

Teratogenic Effects

Reproduction studies have been performed in rabbits, rats, and mice at oral doses up to 100, 150, and 200 mg/kg/day (57, 40, and 27 times the human dose based on mg/m^2), respectively, and revealed no evidence of harm to the fetus due to oxiconazole nitrate. There are, however, no adequate and well-controlled studies in pregnant women. Because animal reproduction studies are not always predictive of human response, this drug should be used during pregnancy only if clearly needed.

Nursing Mothers

Because oxiconazole is excreted in human milk, caution should be exercised when the drug is administered to a nursing woman.

Pediatric Use

Safety and effectiveness in pediatric patients have not been established.

Geriatric Use

A limited number of patients at or above 60 years of age (n ~ 396) have been treated with oxiconazole nitrate cream in US and non-US clinical trials, and a limited number (n = 43) have been treated with OXISTAT Lotion in US clinical trials. The number of patients is too small to permit separate analysis of efficacy and safety. No adverse events were reported with OXISTAT Lotion in geriatric patients, and the adverse reactions reported with oxiconazole nitrate cream in this population were similar to those reported by younger patients. Based on available data, no adjustment of dosage of OXISTAT Lotion in geriatric patients is warranted.

ADVERSE REACTIONS

In a controlled, multicenter clinical trial of 269 patients treated with oxiconazole nitrate lotion, 1%, 7 (2.6%) reported adverse reactions thought to be related to drug therapy. These reactions included burning and stinging (0.7% each) and pruritus, scaling, tingling, pain, and dyshidrotic eczema (0.4% each).

The following additional adverse experiences have been reported with the topical use of oxiconazole nitrate: irritation and allergic contact dermatitis, folliculitis, erythema, papules, fissure, maceration, rash, and nodules.

To report SUSPECTED ADVERSE REACTIONS, contact ANI Pharmaceuticals, Inc. at 1-800-308-6755 or FDA at 1-800-FDA-1088 or www.fda.gov/medwatch.

OVERDOSAGE

When 5% oxiconazole cream (5 times the concentration of the marketed product) was applied at a rate of 1 g/kg to approximately 10% of body surface area of a group of 40 male and female rats for 35 days, 3 deaths and severe dermal inflammation were reported. No overdoses in humans have been reported with use of oxiconazole nitrate cream or lotion.

DOSAGE AND ADMINISTRATION

OXISTAT Lotion should be applied to affected and immediately surrounding areas once to twice daily in patients with tinea pedis, tinea corporis, or tinea cruris. Tinea corporis and tinea cruris should be treated for 2 weeks and tinea pedis for 1 month to reduce the possibility of recurrence. If a patient shows no clinical improvement after the treatment period, the diagnosis should be reviewed.

CLINICAL STUDIES

The following definitions were applied to the clinical and microbiological outcomes in patients enrolled in the clinical trial that form the basis for the approval of OXISTAT Lotion.

Definitions

1. Mycological Cure: No evidence (culture and KOH preparation) of the baseline (original) pathogen in a specimen from the affected area taken at the 2-week post-treatment visit (for tinea [pityriasis] versicolor, mycological cure was limited to KOH only).
2. Treatment Success: Both a global evaluation of 90% clinical improvement and a microbiologic eradication (see above) at the 2-week post-treatment visit.

Tinea Pedis

The clinical trial for the lotion formulation line extension involved 332 evaluable patients with clinically and microbiologically established tinea pedis. Of these evaluable patients, 64% were diagnosed with hyperkeratotic plantar tinea pedis and 28% with interdigital tinea pedis. Seventy-seven percent (77%) had disease secondary to infection with Trichophyton rubrum, 18% had disease secondary to infection with Trichophyton mentagrophytes, and 4% had disease secondary to infection with Epidermophyton floccosum.

The results of this clinical trial at the 2-week post-treatment follow-up visit are shown in the following table:

Patient Outcome | OXISTAT Lotion |  | Vehicle
Patient Outcome | b.i.d. | q.d. | Vehicle
Mycological cure | 67% | 64% | 28%
Treatment success | 41% | 34% | 10%

In this study, the improvement and cure rates of the b.i.d.- and q.d.-treated groups did not differ significantly (95% confidence interval) from each other but were statistically (95% confidence interval) superior to the vehicle-treated group.

HOW SUPPLIED

OXISTAT® (oxiconazole nitrate) Lotion, 1% is supplied in:
30-mL bottle (NDC 62559-285-30)
60-mL bottle (NDC 62559-285-60)

Store at 20° to 25°C (68° to 77°F); excursions permitted at 15° to 30°C (59° to 86°F) [see USP Controlled Room Temperature].

Shake well before using.

OXISTAT is a registered trademark of Fougera Pharmaceuticals, Inc. and is licensed to ANI Pharmaceuticals, Inc.

Distributed by:
ANI Pharmaceuticals, Inc.
Baudette, MN 56623

N7000 Rev 05/22

PACKAGE/LABEL PRINCIPAL DISPLAY PANEL

NDC 62559-285-30
OXISTAT® (oxiconazole nitrate) Lotion, 1%*
*Potency expressed as oxiconazole.
For Topical Dermatologic Use ONLY.
Not for Oral, Ophthalmic or Intravaginal Use.
Rx only
30 mL